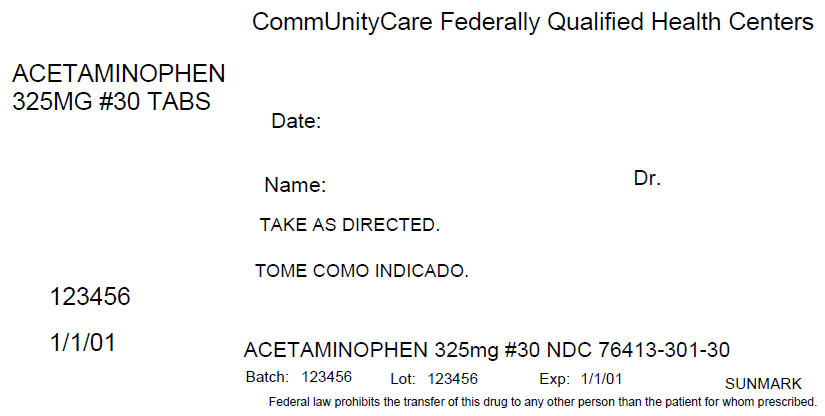 DRUG LABEL: Acetaminophen
NDC: 76413-301 | Form: TABLET, COATED
Manufacturer: Central Texas Community Health Centers
Category: otc | Type: HUMAN OTC DRUG LABEL
Date: 20160309

ACTIVE INGREDIENTS: Acetaminophen 325 mg/1 1
INACTIVE INGREDIENTS: POVIDONES; STARCH, CORN; SODIUM STARCH GLYCOLATE TYPE A CORN; STEARIC ACID

Acetaminophen Tablets

Drug Facts

Active ingredient (in each tablet)

Acetaminophen 325 mg

Purpose

Pain reliever/fever reducer

Uses

- temporarily relieves minor aches and pains due to:
  - headache
  - muscular aches
  - backache
  - minor pain of arthritis
  - the common cold
  - toothache
  - premenstrual and menstrual cramps
- temporarily reduces fever

Warnings

Liver warning

This product contains acetaminophen. Severe liver damage may occur if

- adult takes more than 12 tablets in 24 hours, which is the maximum daily amount
- child takes more than 5 doses in 24 hours
- taken with other drugs containing acetaminophen
- adult has 3 or more alcoholic drinks every day while using this product

Do not use with any other drug containing acetaminophen (prescription or nonprescription). If you are not sure whether a drug contains acetaminophen, ask a doctor or pharmacist.

Ask a doctor before use if the user has liver disease.

Ask a doctor or pharmacist before use if the user is taking the blood thinning drug warfarin

Stop use and ask a doctor if

- pain gets worse or lasts more than 10 days in adults and in children 12 years and over
- pain gets worse or lasts more than 5 days in children under 12 years
- fever gets worse or lasts more than 3 days
- new symptoms occur
- redness or swelling is present

These could be signs of a serious condition.

PREGNANCY OR BREAST FEEDING

If pregnant or breast-feeding, ask a health professional before use.

Keep out of reach of children.

Overdose warning

Taking more than the recommended dose (overdose) may cause liver damage. In case of overdose, get medical help or contact a Poison Control Center right away (1-800-222-1222). Quick medical attention is critical for adults as well as for children even if you do not notice any signs or symptoms.

Directions

- do not take more than directed (see overdose warning)

adults and children 12 years and over | - take 2 tablets every 4 to 6 hours while symptoms last - do not take more than 12 tablets in 24 hours
children 6-11 years | - take 1 tablet every 4 to 6 hours while symptoms last - do not take more than 5 tablets in 24 hours
children under 6 years | - do not use this adult product in children under 6 years of age; this will provide more than the recommended dose (overdose) and may cause liver damage

Other information

- store between 20°-25°C (68°-77°F)
- retain carton for complete product information

Inactive ingredients

crospovidone, methylparaben, povidone, pregelatinized starch, propylparaben, sodium starch glycolate, stearic acid

Distributed By McKesson
One Post Street, San Francisco, CA 94104

PRINCIPAL DISPLAY PANEL - 325 MG Tablet Bottle Label

CommUnityCare Federally Qualified Health Centers

ACETAMINOPHEN
325MG #30 TABS

Date:

Name:
Dr.

TAKE AS DIRECTED.

123456

1/1/01

ACETAMINOPHEN 325mg #30 NDC 76413-301-30

Batch: 123456
Lot: 123456
Exp: 1/1/01
SUNMARK

Federal law prohibits the transfer of this drug to any other person than the patient for whom prescribed.